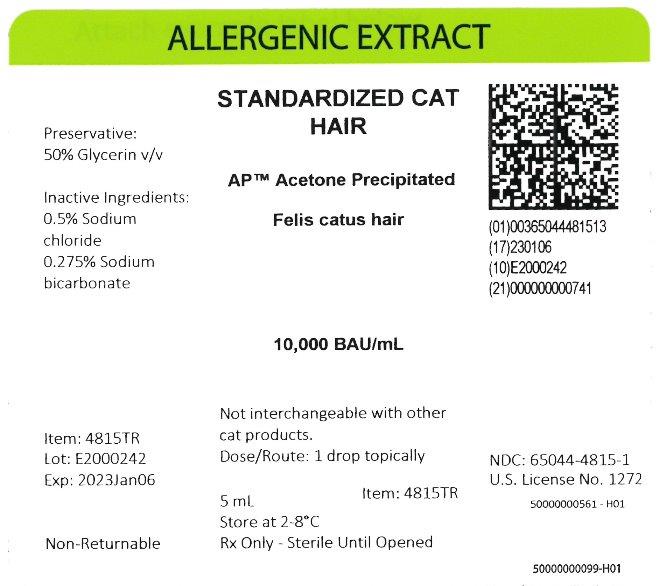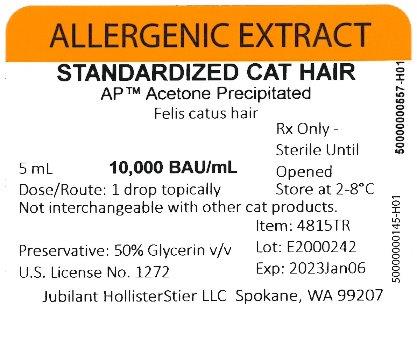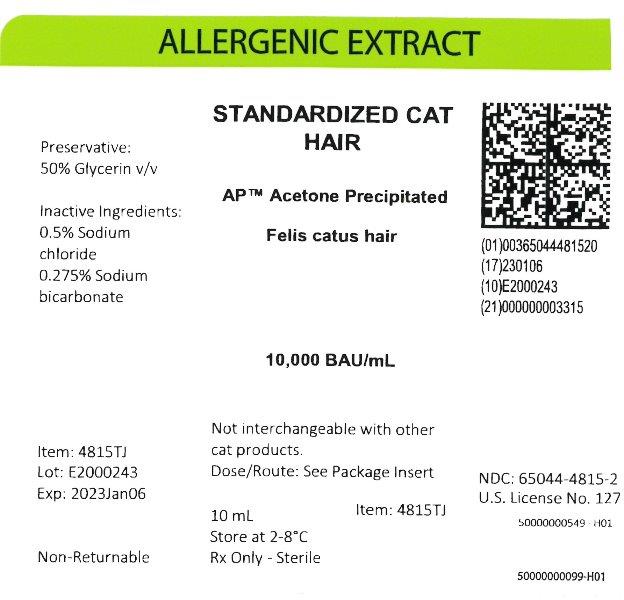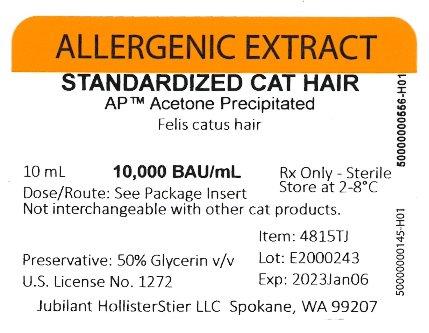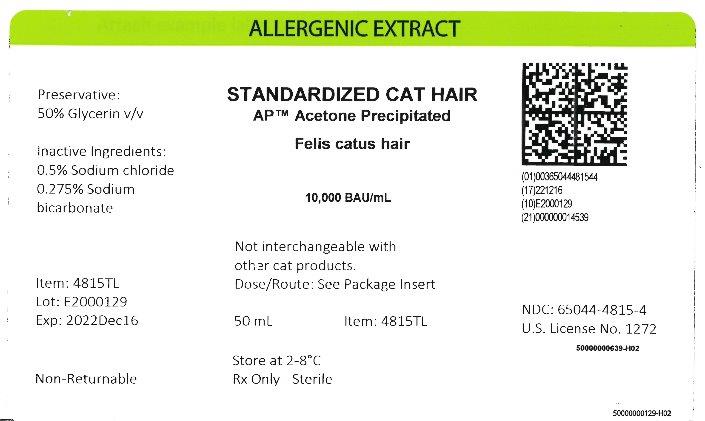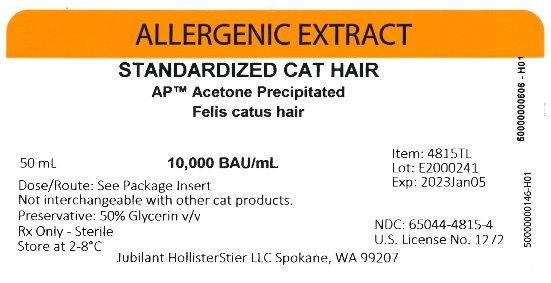 DRUG LABEL: Standardized Cat Hair
NDC: 65044-4815 | Form: INJECTION, SOLUTION
Manufacturer: Jubilant HollisterStier LLC
Category: other | Type: STANDARDIZED ALLERGENIC
Date: 20251119

ACTIVE INGREDIENTS: FELIS CATUS HAIR 10000 [BAU]/1 mL
INACTIVE INGREDIENTS: GLYCERIN; SODIUM BICARBONATE; SODIUM CHLORIDE

ALLERGENIC EXTRACT STANDARDIZED CAT HAIR AP Acetone Precipitated

WARNINGS

This product is intended for use only by licensed medical personnel experienced in administering allergenic extracts and trained to provide immediate emergency treatment in the event of a life-threatening reaction.
Allergenic extracts may potentially elicit a severe life-threatening systemic reaction, rarely resulting in death.1 Therefore, emergency measures and personnel trained in their use must be available immediately in the event of such a reaction. Patients should be instructed to recognize adverse reaction symptoms and cautioned to contact the physician’s office if symptoms occur.
This standardized extract may be more potent than regular extracts and therefore is not directly interchangeable with Jubilant HollisterStier LLC non-standardized extracts, or other manufacturers’ products. Standardized pelt and hair extracts are manufactured from different source materials and are not interchangeable. Standardized cat extracts labeled in AU/mL are not interchangeable with extracts labeled in BAU/mL. See DESCRIPTION Section.
This product should never be injected intravenously.
Refer also to the WARNINGS, PRECAUTIONS, ADVERSE REACTIONS and OVERDOSE Sections for further discussion.

DESCRIPTION

Allergenic extracts are sterile solutions containing the extractables of the source material and components of the extraction fluid. Standardized Cat Hair is available as an extract from acetone precipitated source material in the extraction fluid described below.
Source Material:
Cat Hair Source Material consists of hair clippings and/or shavings which have undergone an acetone precipitation process. AP™ Acetone Precipitated Cat Hair is derived from the precipitate formed when acetone is added to an aqueous extract.
Extracting Fluid:
Glycero-Coca’s: Contains 0.5% sodium chloride, 0.275% sodium bicarbonate, and 50% glycerin (v/v) as a preservative.
Product Concentration:
1. Bioequivalent Allergy Units. When originally licensed, standardized cat extracts containing 10 to 20 Fel d 1 units/mL were arbitrarily assigned 100,000 Allergy Units (AU)/mL. Subsequently, quantitative skin testing by the ID50EAL method 23 was used to determine that standardized cat extracts containing 10 to 19.9 Fel d 1 units/mL should be assigned 10,000 AU/mL rather than 100,000 AU/mL. To avoid possible confusion about this change in allergy unit assignment, the nomenclature changed for cat extracts, and such products are labeled in Bioequivalent Allergy Units (BAU/mL). Each lot of Standardized Cat Hair extract is standardized by quantitating the Fel d 1 content based on standards on file with the Center for Biologics Evaluation and Research (CBER) of the U.S. Food and Drug Administration. Test extracts are diffused in agar containing standard anti-serum to Fel d 1 and compared to the diffusion of a reference cat allergen preparation.2 The potency of the extract is expressed as units of Fel d 1 per mL, and extracts containing 10-19.9 Fel d 1 units per mL are labeled at 10,000 BAU/mL. It has been recognized that there are differences in the levels of non Fel d 1 allergens among standardized cat extracts which utilize different source materials. Isoelectric focusing (IEF) patterns have been shown to be predictive of the presence of non Fel d 1 allergens. Therefore, each lot of Standardized Cat Hair is compared by IEF to a Cat Pelt Extract Reference and a Cat Hair Extract Reference on file with the CBER. The labeled name of the cat extract (i.e., Cat Hair Extract or Cat Pelt Extract) must be supported by matching the IEF profile of the corresponding reference.
2. Concentrate. Concentrate label terminology applies to allergenic extract mixtures where the individual allergens being combined vary in strength or the designation of strength.

e.g. | Concentrate
50% | Short Ragweed 1:20 w/v
25% | Std. Cat Hair 10,000 BAU/mL
25% | Std. Mite D. farinae 10,000 AU/mL

Should the physician choose to calculate the actual strength of each component in the “Concentrate” mixture, the following formulation may be used:

Actual Allergen Strength in Concentrate Mixture | = | Allergen Manufacturing Strength | x | % Allergen in Formulation (by volume or parts

Ingredients:
Active ingredients are the allergen(s) noted on the vial label. Preservative is 50% (v/v) glycerin. Glycerinated extracts contain 0.5% sodium chloride, 0.275% sodium bicarbonate and 50% glycerin (v/v) as a preservative.

CLINICAL PHARMACOLOGY

13 The mechanisms by which hyposensitization is achieved are not completely understood. It has been shown that repeated injections of appropriate allergenic extracts will ameliorate the intensity of allergic symptoms upon contact with the allergen.6, 7, 8, 9 Clinical studies which address the efficacy of immunotherapy are available. The allergens which have been studied are cat, mite, and some pollen extracts.10, 11, 12, 13, 14, 15
IgE antibodies bound to receptors on mast cell membranes are required for the allergic reaction, and their level is probably related to serum IgE concentrations. Immunotherapy has been associated with decreased levels of IgE, and also with increases in allergen specific IgG “ blocking” antibody.
The histamine release response of circulating basophils to a specific allergen is reduced in some patients by immunotherapy, but the mechanism of this change is not yet clear.
The relationships among changes in blocking antibody, reaginic antibody, and mediator-releasing cells, and successful immunotherapy need study and clarification

INDICATIONS AND USAGE

3, 16, 17, 18 Allergenic extracts are indicated for use in diagnosis and immunotherapy of patients presenting symptoms of allergy (hay fever, rhinitis, etc.) to specific environmental allergens. The selection of allergenic extracts to be used should be based on a thorough and carefully taken history of hypersensitivity, and confirmed by skin testing.19, 20
The use of mixed or unrelated antigens for skin testing is not recommended since, in the case of a positive reaction, it does not indicate which component of the mix is responsible for the reaction, while, in the case of a negative reaction, it fails to indicate whether the individual antigens at full concentration would give a positive reaction. Utilization of such mixes for compounding a treatment may result, in the former case, in administering unnecessary antigens and, in the latter case, in the omission of a needed allergen.
Avoidance of allergens is to be advocated if possible, but cannot always be attained, e.g., allergy to cat dander in kennel owners and employees, cat breeders, research workers, veterinarians, etc.
Allergens to which a patient is extremely sensitive should not be included in treatment mixes with allergens to which there is much less sensitivity, but should be administered separately. This allows individualized and better control of dosage increases, including adjustments in dosage becoming necessary after severe reactions which may occur to the highly reactive allergen.

CONTRAINDICATIONS

There are no known absolute contraindications to immunotherapy. However, see PRECAUTIONS for pregnancy risks.
Patients with cardiovascular diseases or pulmonary diseases such as symptomatic asthma, and/or those who are receiving cardiovascular drugs such as beta blockers, may be at higher risk for severe adverse reactions. These patients may also be more refractory to the normal allergy treatment regimen. Patients should be treated only if the benefit of treatment outweighs the risks.1
Treat patients only with allergens to which they are allergic as shown by skin test reaction, have a history of symptoms on exposure to the allergen, and are likely to be exposed again. Any injections, including immunotherapy, should be avoided in patients with a bleeding tendency.
Since there are differences of opinion concerning the possibility of routine immunizations exacerbating autoimmune diseases, immunotherapy should be given cautiously to patients with autoimmune diseases and only if the risk from exposure is greater than the risk of exacerbating the autoimmune process.

WARNINGS

See WARNINGS at the beginning of this instruction sheet.
Allergenic extract should be temporarily withheld from patients or the dose adjusted downward if any of the following conditions exist: (1) severe symptoms of rhinitis and/or asthma; (2) infection or flu accompanied by fever; or (3) exposure to excessive amounts of clinically relevant allergen prior to a scheduled injection. Do not start immunotherapy during a period of symptoms due to exposure. Since the individual components of the extract are those to which the patient is allergic, and to which he will be exposed, typical allergic symptoms may follow shortly after the injection, particularly when the antigen load from exposure plus the injected antigen exceeds the patient’s antigen tolerance.
THE CONCENTRATE SHOULD NOT BE INJECTED AT ANY TIME UNLESS TOLERANCE HAS BEEN ESTABLISHED. DILUTE CONCENTRATED EXTRACTS WITH STERILE DILUENT FOR INTRADERMAL TESTING. INJECTIONS SHOULD NEVER BE GIVEN INTRAVENOUSLY. Subcutaneous injection is recommended. Intracutaneous or intramuscular injection may produce large local reactions or be excessively painful. AFTER INSERTING NEEDLE SUBCUTANEOUSLY, BUT BEFORE INJECTING, ALWAYS WITHDRAW THE PLUNGER SLIGHTLY. IF BLOOD APPEARS IN THE SYRINGE, CHANGE NEEDLE AND GIVE THE INJECTION IN ANOTHER SITE.

BOXED WARNING

IF CHANGING FROM HAIR TO PELT EXTRACTS OR VICE-VERSA: Hair and pelt extracts differ in their non Fel d 1 allergens and are not interchangeable. Therefore, if patients are switched from one type of cat extract to another, the initial dose should be based on skin tests as noted under DOSAGE AND ADMINISTRATION, 3. Immunotherapy.
IF THE PREVIOUS EXTRACT WAS NON-STANDARDIZED OR WAS STANDARDIZED AND LABELED IN ALLERGY UNITS PER mL (AU/mL): This standardized extract may be more potent than non-standardized extracts. Initiate therapy as though patient had not been receiving immunotherapy, or determine initial dose by skin test using serial dilutions of the extract. See PRECAUTIONS and DOSAGE AND ADMINISTRATION Sections.
IF CHANGING TO A DIFFERENT LOT OF JUBILANT HOLLISTERSTIER EXTRACT: Even though it is the same formula and concentration, the first dose of the new extract should not exceed 50% of the last administered dose from the previous extract.
IF THE EXTRACT PREVIOUSLY USED WAS FROM ANOTHER MANUFACTURER: Since manufacturing processes and sources of raw materials differ among manufacturers, the interchangeability of extracts from different manufacturers cannot be insured. The starting dose of the extract therefore should be greatly decreased even though the extract is the same formula and dilution. Initiate therapy as though patient had not been receiving immunotherapy, or determine initial dose by skin test using serial dilutions of the extract. See DOSAGE AND ADMINISTRATION and ADVERSE REACTIONS Sections.
IF A PROLONGED PERIOD OF TIME HAS ELAPSED SINCE THE LAST INJECTION: Patients may lose tolerance for allergen injections during prolonged periods between doses. The duration of tolerance is an individual characteristic and varies from patient to patient. In general, the longer the lapse in the injection schedule, the greater dose reduction required. If the interval since last dose is over four weeks, perform skin tests to determine starting dose.
IF THE PREVIOUS EXTRACT WAS OUTDATED: The dating period for allergenic extracts indicates the time that they can be expected to remain potent under refrigerated storage conditions (2° - 8° C). During the storage of extracts, even under ideal conditions, some loss of potency occurs. For this reason, extracts should not be used beyond their expiration date. If a patient has been receiving injections of an outdated extract, he may experience excessive local or systemic reactions when changed to a new, and possibly more potent, extract. In general, the longer the material has been outdated, the greater the dose reduction necessary for the fresh extract.
IF CHANGING FROM ALUM-ADSORBED TO AQUEOUS OR GLYCERINATED EXTRACTS: When the patient previously has been receiving alum-adsorbed or alum-precipitated extract, the safest course is to start over as though the patient had not been receiving immunotherapy. See DOSAGE AND ADMINISTRATION and ADVERSE REACTIONS in product instructions.
IF ANY OTHER CHANGES HAVE BEEN MADE IN THE EXTRACT CONCENTRATE FORMULA: Changes other than those listed above may include situations such as a redistribution of component parts or percentages, a difference in extracting fluid (i.e., change from non-glycerin extracts to 50% glycerin extracts), combining two or more stock concentrates, or any other change.
It should be recognized that any change in formula can affect a patient’s tolerance of the treatment. The usual 1/2 of the previous dose for a new extract may produce an adverse reaction: extra dilutions are recommended whenever starting a revised formula. The greater the change, the greater the number of dilutions required.

WARNINGS

Proper selection of the dose and careful injection should prevent most systemic reactions. It must be remembered, however, that allergenic extracts are highly potent in sensitive individuals, and that systemic reactions of varying degrees of severity may occur, including urticaria, rhinitis, conjunctivitis, wheezing, coughing, angioedema, hypotension, bradycardia, pallor, laryngeal edema, fainting, or even anaphylactic shock and death. Patients should be informed of this, and the precautions should be discussed prior to immunotherapy. (See PRECAUTIONS below.) Severe systemic reactions should be treated as indicated in the ADVERSE REACTIONS Section.

PRECAUTIONS

(1) General

Concentrated extracts must be diluted prior to use: See DOSAGE AND ADMINISTRATION Section below for detailed instructions on the dilution of allergenic extracts.
Any evidence of a local or generalized reaction requires a reduction in dosage during the initial stages of immunotherapy, as well as during maintenance therapy.
Allergenic extracts diluted with sterile Albumin Saline with Phenol (0.4%) diluent may be more potent than extracts diluted with diluents which do not contain stabilizers. When changing from non-stabilized to stabilized diluent, consider weaker initial dilutions for both intradermal testing and immunotherapy.
Sterile solutions, vials, syringes, etc. should be used and aseptic precautions observed in making dilutions.
To avoid cross-contamination, do not use the same needle to withdraw materials from vials of more than one extract, or extract followed by diluent.
A sterile tuberculin syringe graduated in 0.01 mL units should be used to measure each dose from the appropriate dilution. Aseptic techniques should always be employed when injections of allergenic extracts are being administered.
A separate sterile syringe should be used for each patient to prevent transmission of serum hepatitis and other infectious agents from one person to another.
Patient reactions to previous injections should be reviewed before each new injection. A conservative dosage schedule should be followed by the physician until a pattern of local responses is established which can be used to monitor increases in dosage.
Rarely, a patient is encountered who develops systemic reactions to minute doses of allergen and does not demonstrate increasing tolerance to injections after several months of treatment. If systemic reactions or excessive local responses occur persistently at very small doses, efforts at immunotherapy should be stopped.
PATIENTS SHOULD BE OBSERVED IN THE OFFICE FOR 30 MINUTES AFTER EACH TREATMENT INJECTION. Most severe reactions will occur within this time period, and rapid treatment measures should be instituted. See ADVERSE REACTIONS Section for such treatment measures.

(2) Information for Patients

Patients should be instructed in the recognition of adverse reactions to immunotherapy, and in particular, to the symptoms of shock. Patients should be made to understand the importance of a 30 minute observation period, and be warned to return to the office promptly if symptoms occur after leaving.

(3)Drug Interactions

Patients on non-selective beta blockers may be more reactive to allergens given for testing or treatment and may be unresponsive to the usual doses of epinephrine used to treat allergic reactions.5
Certain medications may lessen the skin test wheal and erythema responses elicited by allergens and histamine for varying time periods. Conventional antihistamines should be discontinued at least 5 days before skin testing. Long acting antihistamines should be discontinued for at least 3 weeks prior to skin testing.24 Topical steroids should be discontinued at the skin test site for at least 2-3 weeks before skin testing.24, 25
Tricyclic antidepressants such as Doxepin should be withheld for at least 7 days before skin testing. 26 Topical local anesthetics may suppress the fl are responses and should be avoided in skin test sites.27

(4) Carcinogenesis, Mutagenesis, Impairment of Fertility

Long-term studies in animals have not been conducted with allergenic extracts to determine their potential for carcinogenicity, mutagenicity or impairment of fertility.

(5) Pregnancy

Animal reproduction studies have not been conducted with allergenic extracts. It is also not known whether allergenic extracts can cause fetal harm when administered to a pregnant woman or can affect reproduction capacity. Allergenic extracts should be given to a pregnant woman only if clearly needed.
For women who have been getting maintenance doses of allergen without side effect, the occurrence of pregnancy is not an indication to stop immunotherapy.

(6) Nursing Mothers

There are no current studies on secretion of the allergenic extract components in human milk or effect on the nursing infant. Because many drugs are excreted in human milk, caution should be exercised when allergenic extracts are administered to a nursing woman.

(7) Pediatric Use

Since dosage for the pediatric population is the same as for adults 3,4 the larger volumes of solution may produce excessive discomfort. Therefore, in order to achieve the total dose required, the volume
of the dose may need to be divided into more than one injection per visit.

(8) Geriatric Use

The reactions from immunotherapy can be expected to be the same in elderly patients as in younger ones. Elderly patients may be more likely to be on medication that could block the effect of epinephrine which could be used to treat serious reactions, or they could be more sensitive to the cardiovascular side effect of epinephrine because of pre-existing cardiovascular disease.26

ADVERSE REACTIONS

1. Local Reactions
Some erythema, swelling or pruritus at the site of injection are common, the extent varying with the patient. Such reactions should not be considered significant unless they persist for at least 24 hours. Local reactions (erythema or swelling) which exceed 4-5 cm in diameter are not only uncomfortable, but also indicate the possibility of a systemic reaction if dosage is increased. In such cases the dosage should be reduced to the last level not causing the reaction and maintained at this level for two or three treatments before cautiously increasing again.
Large persistent local reactions may be treated by local cold, wet dressings and/or the use of oral antihistamines. They should be considered a warning of possible severe systemic reactions and an indication of the need for temporarily reduced dosages.
A mild burning immediately after the injection is to be expected. This usually leaves in 10 to 20 seconds.
2. Systemic Reactions
With careful attention to dosage and administration, systemic reactions occur infrequently, but it cannot be overemphasized that in sensitive individuals, any injection could result in anaphylactic shock. Therefore, it is imperative that physicians administering allergenic extracts understand and be prepared for the treatment of severe reactions.
Other possible systemic reactions which may occur in varying degrees of severity are laryngeal edema, fainting, pallor, bradycardia, hypotension, angioedema, cough, wheezing, conjunctivitis, rhinitis, and urticaria. adverse reaction frequency data for allergenic extract administration for testing and treatment show that risk is low.1,21
If a systemic or anaphylactic reaction does occur, apply a tourniquet above the site of injection and inject 1:1000 epinephrine-hydrochloride intramuscularly or subcutaneously into the opposite arm. Loosen the tourniquet at least every 10 minutes. Do not obstruct arterial blood flow with the tourniquet.
EPINEPHRINE DOSAGE
ADULT: 0.3 to 0.5 mL should be injected. Repeat in 5 to 10 minutes if necessary.
PEDIATRIC: The usual initial dose is 0.01 mg (mL) per kg body weight or 0.3 mg (mL) per square meter of body surface area. Suggested dosage for infants to 2 years of age is 0.05 mL to 0.1 mL; for children 2 to 6 years, 0.15 mL; and children 6 to 12 years, 0.2 mL. Single pediatric doses should not exceed 0.3 mg (mL). Doses may be repeated as frequently as every 20 minutes, depending on the severity of the condition and the response of the patient.
After administration of epinephrine, profound shock or vasomotor collapse should be treated with intravenous fluids, and possibly vasoactive drugs. Airway patency should be insured. Oxygen should be given by mask. Intravenous antihistamine, theophylline and/or corticosteroids may be used if necessary after adequate epinephrine and circulatory support has been given.
Emergency resuscitation measures and personnel trained in their use must be available immediately in the event of a serious systemic or anaphylactic reaction not responsive to the above measures [Ref. J. Allergy and Clinical Immunology, 77(2):p. 271-273, 1986].
Rarely are all of the above measures necessary; the tourniquet and epinephrine usually produce prompt responses. However, the physician should be prepared in advance for all contingencies. Promptness in beginning emergency treatment measures is of utmost importance.
Severe systemic reactions mandate a decrease of at least 50% in the next dose, followed by cautious increases. Repeated systemic reactions, even of a mild nature, are sufficient reason for the cessation of further attempts to increase the reaction-causing dose.
3. Adverse Event Reporting
Report all adverse events to Jubilant HollisterStier LLC Customer Technical Services Department at 1 (800) 992-1120. A voluntary adverse event reporting system for health professionals is available through the FDA MEDWATCH program. Preprinted forms (FDA Form 3500) are available from the FDA by calling 1 (800) FDA-1088. Completed forms should be mailed to MEDWATCH, 5600 Fisher Lane, Rockville, MD 20852-9787 or Fax to: 1 (800) FDA-0178.

OVERDOSAGE

See ADVERSE REACTIONS Section

DOSAGE AND ADMINISTRATION

3, 16, 17, 18
(1) General
Sterile aqueous diluent containing human serum albumin is recommended when preparing dilutions of the concentrate for intradermal testing or immunotherapy. Dilutions should be made accurately and aseptically, using sterile diluent, vials, syringes, etc. Mix thoroughly and gently by rocking or swirling. Parenteral drug products should be inspected visually for particulate matter and discoloration prior to administration whenever solution and container permit.
(2) Diagnosis
To identify highly sensitive individuals and as a safety precaution, it is recommended that a prick or puncture test using a drop of the extract concentrate be performed prior to initiating intradermal testing. Prick tests are performed by placing a drop of extract on the skin and piercing through the drop into the skin with a slight lifting motion. Puncture tests are performed by placing a drop of extract on the skin and piercing through the drop perpendicular to the skin with a device such as a Prick Lancetter. After about 1 minute the extract may be wiped away with a dry sponge. The diameter of wheal and erythema reactions are measured 15 minutes after the prick or puncture is made, and the sensitivity class of the patient determined by the table presented at the end of the diagnosis section. Less sensitive individuals (Class 0 to 1+) can be tested intradermally with the recommended dilutions of the extract concentrate (see intradermal testing information below). The skin test concentration of 10,000 BAU/mL (10-19.9 Fel d 1 units/mL) in dropper vials is used for prick or puncture testing. Puncture tests performed on 15 highly sensitive subjects showed the following:

Product | Mean Sum of Wheal ± Std. Dev. (mm) | Mean Sum of Erythema ± 1 Std. Dev. (mm)
Standardized Cat Hair | 15.1 ± 3.8 | 73.3 ± 14.3

The sum of a skin response is the sum of the longest diameter and the midpoint orthogonal diameter.
Intradermal endpoint titration (IET) tests were completed using the same 15 subjects to determine the mean concentration required to produce a ∑E of 50mm (D50). That concentration contained 0.049 BAU/mL (range 0.006 to 0.661 BAU/mL). Intradermal extract should be used as follows: Intradermal Tests should be done only on patients with a negative prick or puncture test. Patients who do not react to a valid prick or puncture test should be tested intradermally with 0.02 to 0.05 mL of a 100 BAU/mL extract solution. If this test is negative, a second intradermal test may be performed using a 1,000 BAU/mL extract solution. If the intradermal dilutions were prepared from glycerinated concentrate, the negative control used with this latter dilution should contain 5% glycerol. Skin tests are graded in terms of the wheal and erythema response noted at 15 minutes. Wheal and erythema size may be recorded by actual measurement of the extent of both responses. Refer to the following table to determine the skin test sensitivity class. The corresponding ∑E (sum of the longest diameter and the mid-point orthogonal diameters of erythema) is also presented.

Class | Wheal Diameter | Erythema Diameter | Corresponding ∑E
0 | < 5 mm | <5 mm | <10 mm
± | 5-10 mm | 5-10 mm | 10-20 mm
1+ | 5-10 mm | 11-20 mm | 20-40 mm
2+ | 5-10 mm | 21-30 mm | 40-60 mm
3+ | 10-15 mm a | 31-40 mm | 60-80 mm
4+ | >15 mm b | >40 mm | >80 mm

a. or with pseudopods
b. or with many pseudopods
3) Immunotherapy
Allergen extracts should be administered using a sterile syringe with 0.01 mL gradations and a 25-27 gauge x 1/2" to 5/8" needle. The injections are given subcutaneously. The most common sites of injection are the lateral aspect of the upper arm or thigh. Intracutaneous or intramuscular injections may produce large local reactions which may be very painful. Dosage of allergenic extracts is a highly individualized matter and varies according to the degree of sensitivity of the patient, his clinical response, and tolerance to the extract administered during the early phases of an injection regimen. The starting dose should be based on skin tests of the extract to be used for immunotherapy. To prepare dilutions for intradermal and therapeutic use, make a 1:10 dilution by adding 1.0 mL of the concentrate to 9.0 mL of sterile aqueous diluent. Subsequent serial dilutions are made in a similar manner. (See Table I.) To determine the starting dose, begin intradermal testing with the most dilute extract preparation. Inject 0.02 mL and read the reaction after 15 minutes. Intradermal testing is continued with increasing concentrations of the extract until a reaction of 10-20 mm erythema (∑E 20-40 mm) and/or a 5 mm wheal occurs. This concentration at a dose of 0.03 mL then can serve as a starting dose for immunotherapy and be increased by 0.03 mL to as high as 0.12 mL increments each time until 0.3 mL is reached, at which time a dilution 10 times as strong can be used, starting with 0.03 mL. Proceed in this way until a tolerance dose is reached or symptoms are controlled. Suggested maintenance dose is 0.2 mL of the concentrate. Occasionally, higher doses are necessary to relieve symptoms. Special caution is required in administering doses greater than 0.2 mL. The interval between doses normally is 3 to 7 days. This is offered as a suggested schedule for average patients and will be satisfactory in most cases. However, the degree of sensitivity varies in many patients. The size of the dose should be adjusted and should be regulated by the patient’s tolerance and reaction. The size of the dose should be decreased if the previous injection resulted in marked local or the slightest general reaction. Another dose should never be given until all local reactions resulting from the previous dose have disappeared. In some patients, the dosage may be increased more rapidly than called for in the schedule. In seasonal allergies, treatment should be started and the interval between doses regulated so that at least the first 20 doses will have been administered by the time symptoms are expected. Thus, the shorter the interval between the start of immunotherapy and the expected onset of symptoms, the shorter the interval between each dose. Some patients may even tolerate daily doses. A maintenance dose, the largest dose tolerated by the patient that relieves symptoms without producing undesirable local or general reactions is recommended for most patients. The upper limits of dosage have not been established; however, doses larger than 0.2 mL of the glycerinated concentrate may be painful due to the glycerin content. The dosage of allergenic extract does not vary significantly with the respiratory allergic disease under treatment. The size of this dose and the interval between doses will vary and can be adjusted as necessary. Should symptoms develop before the next injection is scheduled, the interval between doses should be decreased. Should allergic symptoms or local reactions develop shortly after the dose is administered, the size of the dose should be decreased. In seasonal allergies, it is often advisable to decrease the dose to one-half or one-quarter of the maximum dose previously attained if the patient has any seasonal symptoms. The interval between maintenance doses can be increased gradually from one week to 10 days, to two weeks, to three weeks, or even to four weeks if tolerated. Repeat the doses at a given interval three or four times to check for untoward reactions before further increasing the interval. Protection is lost rapidly if the interval between doses is more than four weeks. (See WARNINGS Section.) The usual duration of treatment has not been established. A period of two or three years of injection therapy constitutes an average minimum course of treatment.

TABLE 1
TEN-FOLD DILUTION SERIES
Standardized Extracts Labeled 10,000 BAU/mL

Dilution | Extract | + Diluent | = | BAU/mL Concentration
0 | Concentrate | +0 mL | = | 10,000
1 | 1 mL concentrate | +9 mL | = | 1,000
2 | 1 mL dilution #1 | +9 mL | = | 100
3 | 1 mL dilution #2 | +9 mL | = | 10
4 | 1 mL dilution #3 | +9 mL | = | 1
5 | 1 mL dilution #4 | +9 mL | = | 0.1
6 | 1 mL dilution #5 | +9 mL | = | 0.01
7 | 1 mL dilution #6 | +9 mL | = | 0.001

(4) Pediatric Use

(See PRECAUTIONS)

HOW SUPPLIED

Standardized Cat Hair allergenic extract is supplied for diagnostic and therapeutic use:
Diagnostics:
Prick or puncture testing, 10,000 BAU/mL [50% glycerin (v/v)] in 5 mL dropper vial.
Bulk Therapeutics, multiple dose vials in 50% glycerin (v/v).
10 mL vial, 10,000 BAU/mL
30 mL vial, 10,000 BAU/mL
50 mL vial, 10,000 BAU/mL

STORAGE

The expiration date of the Standardized Cat Hair extract containing 10,000 BAU/mL is listed on the container label. The extract should be stored at 2° - 8° C. Dilutions of the BAU/mL concentrates are less stable and, if loss of potency is suspected, should be checked by skin testing with equal bioequivalent allergy units of a freshly prepared dilution on known cat allergic individuals.

LIMITED WARRANTY

A number of factors beyond our control could reduce the efficacy of this product or even result in an ill effect following its use. These include storage and handling of the product after it leaves our hands, diagnosis, dosage, method of administration and biological differences in individual patients. Because of these factors, it is important that this product be stored properly and that the directions be followed carefully during use.

The foregoing statement is made in lieu of any other warranty of merchantability or fitness. Representatives of the Company are not authorized to vary the terms of this warranty or the contents of any printed labeling for this product except by printed notice from the Company’s headquarters. The prescriber and user of this product must accept the terms hereof.

REFERENCES

1. Lockey, Richard F., Linda M. Benedict, Paul C. Turkeltaub, Samuel C. Bukantz. Fatalities from immunotherapy (IT) and skin testing (ST). J. Allergy Clin. Immunol. 79 (4): 660-677, April 1987.
2. Assay for Cat Allergen I. Manual of Methods, Laboratory of Allergenic Products, Center for Biologics Evaluation and Research. Sept. 1984.
3. Patterson, Roy, et al. Allergy Principles and Practice, 2nd ed. E. Middleton, Jr., C.E. Reed, E.F. Ellis, Ed. C.V. Mosby Co., St. Louis, MO, 1983, Chapter 52.
4. Levy, D.A., L.M. Lichtenstein, E.O. Goldstein, K. Ishizaka. Immunologic and cellular changes accompanying the therapy of pollen allergy. J. Clinical Investigation. 50:360, 1971.
5. Jacobs, R.L., G.W. Rake, Jr., et al. Potentiated anaphylaxis in patients with drug-induced beta-adrenergic blockade. J. Allergy and Clin. Immunol. 68 (2): 125-127, August 1981.
6. Lowell, F.C., W. Franklin. A “double-blind” study of treatment with aqueous allergenic extracts in cases of allergic rhinitis. J. Allergy. 34 (2): 165-182, 1983.
7. Lowell, F.C., W. Franklin. A double-blind study of the effectiveness and specificity of injection therapy in ragweed hay fever. N. Eng. J. Med. 273 (13): 675-679, 1965.
8. Zavazal, V., A. Stajner. Immunologic changes during specific treatment of the atopic state. II. Acta. Allergol. 25 (1): 11-17, 1970.
9. Reisman, R.E., J.I. Wypych, E.E. Arbesman. Relationships of immunotherapy, seasonal pollen exposure and clinical response to serum concentrations of total IgE and ragweed-specific IgE. Int. Arch. Allergy Appl. Immunol. 48 (6): 721-730, 1975.
10. Ohman, J.L., S.R. Findlay, K. Leiterman. Immunotherapy in cat-induced asthma: double-blind trial with evaluation of in vivo and vitro responses. J. Allergy Clin. Immunol. 74:230, 1984.
11. Sundin, B., G. Lilja, V. Graff-Lonnevig, G. Hedlin, H. Heilborn, K. Norrlind, K-O Pegelow, H. Lowenstein. Immunotherapy with partially purified and standardized animal dander extracts. I Clinical results from a double-blind study on patients with animal dander asthma. J. Allergy Clin. Immunol. 77:478, 1986.
12. Chapman, M.D., T.A.E. Platts-Mills, M. Gabriel, H.K. Ng, W.G.L. Allen, L.E. Hill, A.J. Nunn. Antibody response following prolonged hyposensitization with Dermatophagoides pteronyssinus extract. Int. Arch. Allergy Appl. Immunol. 61: 431-440, 1980.
13. Norman, P.S. Postgraduate Course Presentation. An overview of immunotherapy, implications for the future. J. Allergy Clin. Immunol, 65 (2): 87-96, 1980.
14. Norman, P.S., W.L. Winkenwerder. Maintenance immunotherapy in ragweed hay fever. J. Allergy, 74: 273-282, 1971.
15. Norman, P.S., W.L. Winkenwerder, L.M. Lichtenstein. Immunotherapy of hay fever with ragweed Antigen E; comparisons with whole pollen extract and placebos. J. Allergy. 42: 93-108, 1968.
16. Sheldon, J.M., R.G. Lovell, K.P. Matthews. A Manual of Clinical Allergy. Second Edition. W.B. Saunders. Philadelphia, 1967, pp. 107-112.
17. Sherman, W.B. Hypersensitivity Mechanism and Management. W.B. Sanders, Philadelphia, 1968, pp. 169-172.
18. Swineford, O. Asthma and Hay Fever. Charles C. Thomas. Springfield, IL, 1971, pp. 148-155.
19. Pauli, G., J.C. Bessot, R. Thierry, A. Lamensons. Correlation between skin, inhalation tests and specific IgE in a study of 120 subjects to house dust and D. pteronyssinus. Clin. Allergy. 7:337, 1977.
20. Murray, A.B., A.C. Ferguson, B.J. Morrison. Diagnosis of house dust mite allergy in asthmatic children: What constitutes positive history? J. Allergy Clin. Immunol. 71:21, 1983.
21. Turkeltaub, Paul C., Peter J. Gergen. The risk of adverse reactions from percutaneous prick-puncture allergen skin testing, venipuncture, and body measurements: Data from the second National Health and Nutrition Examination Survey 1976-80 (NHANES II). J. Allergy Clin. Immunol. 84 (6): 886-890, Dec. 1989.
22. Metzger, W.J., E. Turner, R. Patterson. The safety of immunotherapy during pregnancy. J. Allergy Clin. Immunol. 61 (4): 268-272. 1978.
23. Turkeltaub, Paul C., Suresh Rastogi, Harold Baer. Skin test method for evaluation of subject sensitivity to standardized allergenic extracts and for assignment of Allergy Units to reference preparations using the ID50EAL Method. Manual of Methods, Center for Biologics Evaluation and Research. May 1986.
24. Pipkorn, Ulf. Pharmacological influence of anti-allergic medication on In Vivo allergen testing. Allergy. 43: 81-86, 1988.
25. Andersson, M. and U. Pipkorn. Inhibition of the dermal immediate allergic reaction through prolonged treatment with topical glucocorticosteroids. Journal Allergy Clinical Immunology. 79 (2): 345-349, February 1987.
26. Rao, Kamineni S., et al. Duration of suppressive effect of tricyclic anti-depressants on histamine induced wheal and flare reactions on human skin. Journal Allergy Clinical Immunology. 82: 752-757, November 1988.
27. Pipkorn, Ulf, M. Andersson. Topical dermal anesthesia inhibits the fl are but not the wheal response to allergen and histamine in the skin prick test. Clinical Allergy. 17: 307-311, 1987